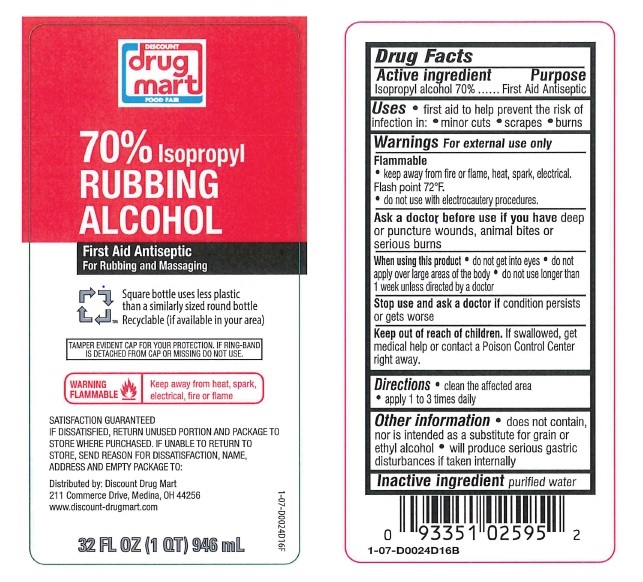 DRUG LABEL: Isopropyl Rubbing Alcohol
NDC: 53943-070 | Form: SOLUTION
Manufacturer: Discount Drug Mart
Category: otc | Type: HUMAN OTC DRUG LABEL
Date: 20260112

ACTIVE INGREDIENTS: ISOPROPYL ALCOHOL 70 mL/100 mL
INACTIVE INGREDIENTS: WATER

Isopropyl Alcohol

Active Ingredient

Isopropyl Alcohol 70%

Purpose

First Aid Antiseptic

Warnings

For external use only

Flammable

Keep away from fire or flame, heat, spark, electrical

Do not use with electrocautery procedures

Ask a doctor before use if you have deep or puncture wounds, animal bites or serious burns

When using this product

do not get into eyes

do ot apply over large areas of the body

do not use longer than 1 week unless directed by a doctor

Stop use and ask a doctor if condition persists or gets worse

Keep out of reach of children.

If swallowed, get medical help or contact a Poison Control Center right away

Directions

Clean the affected area

Apply a small amount of this product 1 to 3 times daily

May be covered with a sterile bandage

If bandaged, let dry first

Other Information

Does not contain, nor is intended as a substitute for grain or ethyl alcohol

Will produce serious gastric disturbances if taken internally

Inactive Ingredient

purified water

PACKAGE LABEL

Discount Drug Mart

70% Isopropyl Rubbing Alcohol

First Aid Antiseptic

For Rubbing and Massaging

Square bottle uses less plastic than a similarly sized round bottle

Recycleable (if available in your area)

TAMPER EVIDENT CAP FOR YOUR PROTECTION. IF RING-BAND IS DETACHED FROM CAP OR MISSING DO NOT USE.

WARNING FLAMMABLE

Keep away from heat, spark, electrical, fire or flame

Satisfaction Guaranteed

IF DISSATISFIED, RETURN UNUSED PORTION AND PACKAGE TO STORE WHERE PURCHASED. IF UNABLE TO RETURN TO STORE, SEND REASON FOR DISSATISFACTION, NAME, ADDRESS AND EMPTY PACKAGE TO:

Distributed by: Discount Drug Mart

211 Commerce Drive, Medina, OH 44256

www.discount-drugmart.com

32 FL OZ (1 QT)